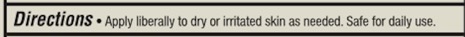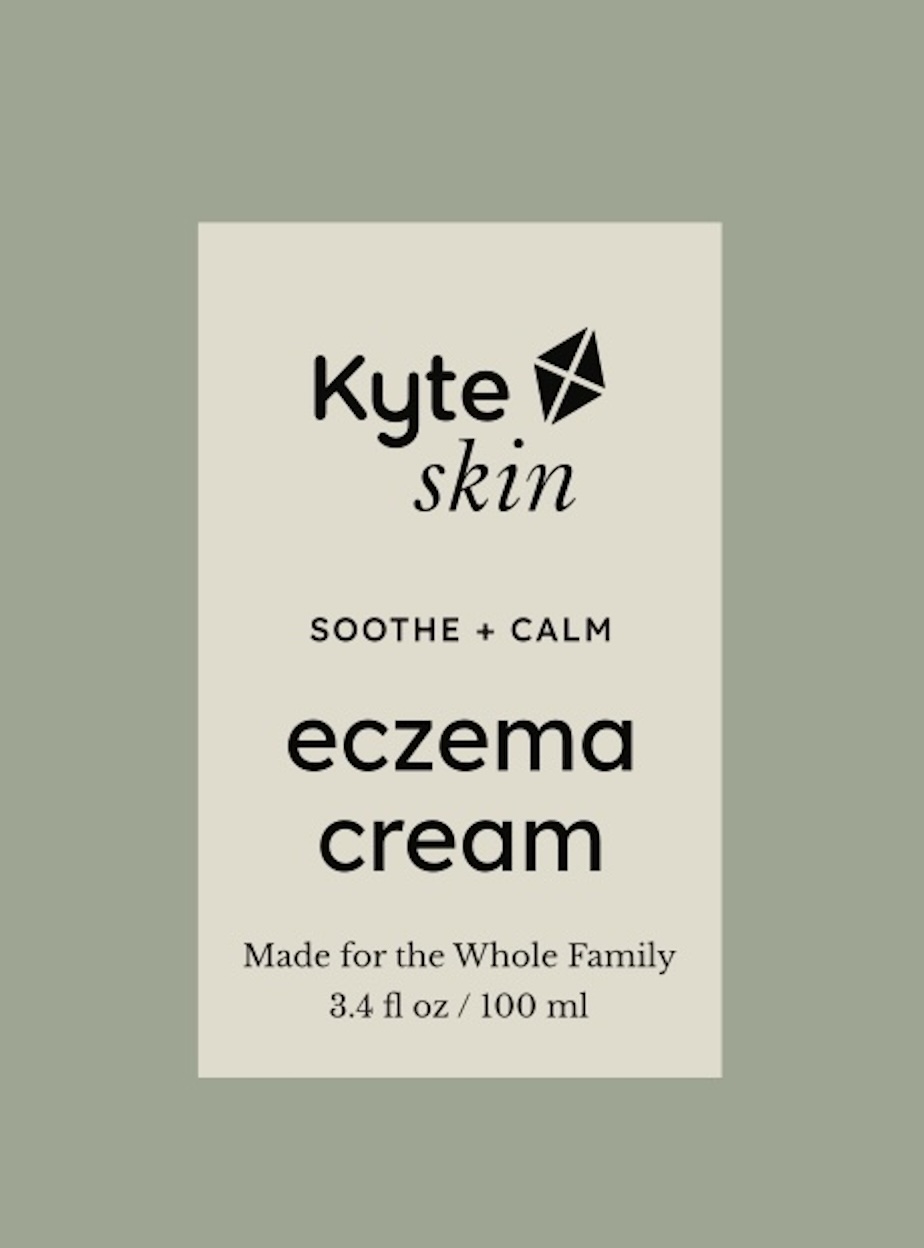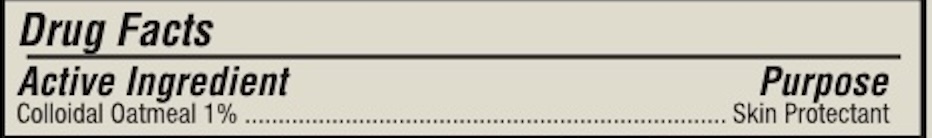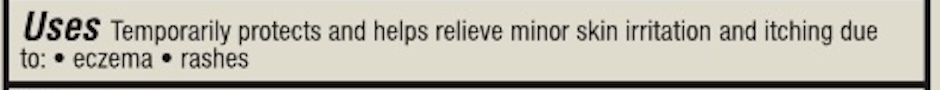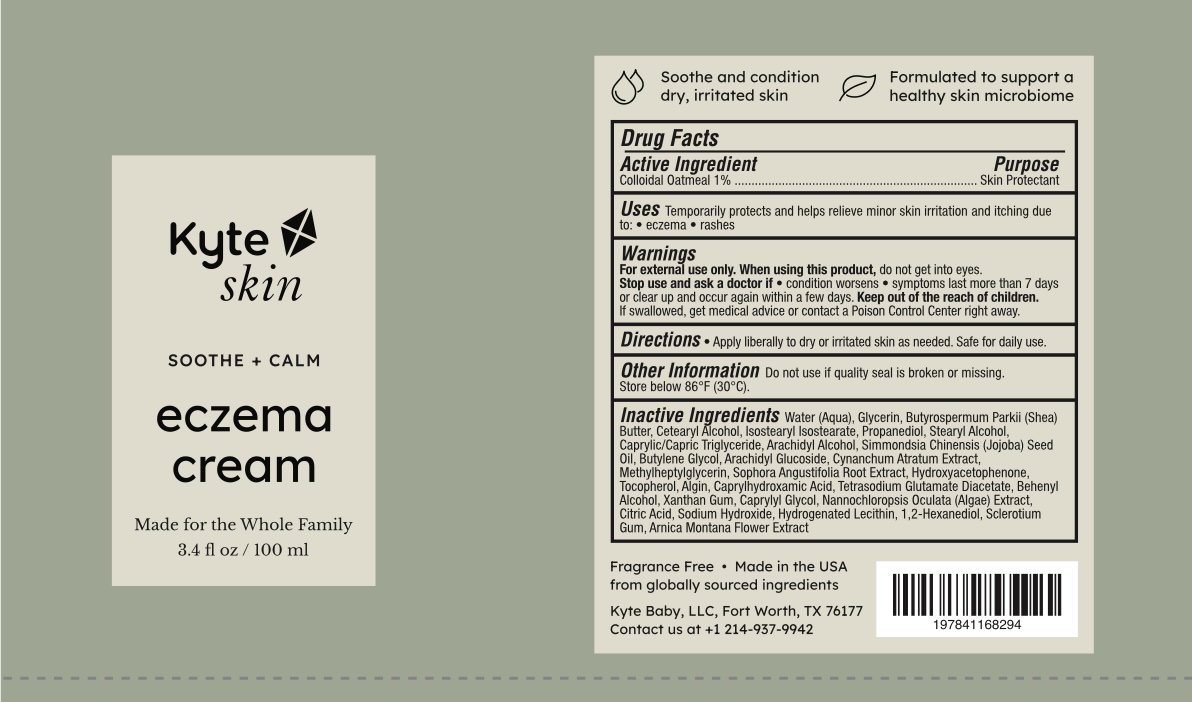 DRUG LABEL: Eczema Cream
NDC: 85303-001 | Form: CREAM
Manufacturer: Kyte Baby LLC
Category: otc | Type: HUMAN OTC DRUG LABEL
Date: 20250320

ACTIVE INGREDIENTS: OATMEAL 1 g/100 mL
INACTIVE INGREDIENTS: XANTHAN GUM; ARACHIDYL ALCOHOL; BUTYLENE GLYCOL; ARACHIDYL GLUCOSIDE; TOCOPHEROL; TETRASODIUM GLUTAMATE DIACETATE; BEHENYL ALCOHOL; PROPANEDIOL; CAPRYLYL GLYCOL; ISOSTEARYL ISOSTEARATE; STEARYL ALCOHOL; CITRIC ACID; CAPRYLHYDROXAMIC ACID; CETEARYL ALCOHOL; CAPRYLIC/CAPRIC TRIGLYCERIDE; SIMMONDSIA CHINENSIS (JOJOBA) SEED OIL; VINCETOXICUM ATRATUM WHOLE; HYDROXYACETOPHENONE; ALGIN; SOPHORA FLAVESCENS ROOT; SODIUM HYDROXIDE; WATER; GLYCERIN; BUTYROSPERMUM PARKII (SHEA) BUTTER; NANNOCHLOROPSIS OCULATA; METHYLHEPTYLGLYCERIN; HYDROGENATED SOYBEAN LECITHIN

Warnings

For external use only. When using this product, do not get into eyes.

Stop use and ask a doctor if condition worsens • symptoms last more than 7 days or clear up and occur again within a few days. Keep out of the reach of children.

If swallowed, get medical advice or contact a Poison Control Center right away.

Keep out of the reach of children.

If swallowed, get medical advice or contact a Poison Control Center right away.

INACTIVE INGREDIENT

Inactive Ingredients Water (Aqua), Glycerin, Butyrospermum Parkii (Shea Butter, Cetearyl Alcohol, Isostearyl Isostearate, Propanediol, Stearyl Alcohol.

Caprylic/Capric Triglyceride, Arachidyl Alcohol, Simmondsia Chinensis (Jojoba) Seed Oil, Butylene Glycol, Arachidyl Glucoside, Cynanchum Atratum Extract, Methylheptyglycerin, Sophora Angustifolia Root Extract, Hydroxyacetophenone, Tocopherol, Algin, Caprylhydroxamic Acid, Tetrasodium Glutamate Diacetate, Behenyl Alcohol, Xanthan Gum, Caprylyl Glycol, Nannochloropsis Oculata (Algae) Extract, Citric Acid, Sodium Hydroxide, Hydrogenated Lecithin, 1,2-Hexanediol, Sclerotium

Gum, Arnica Montana Flower Extract